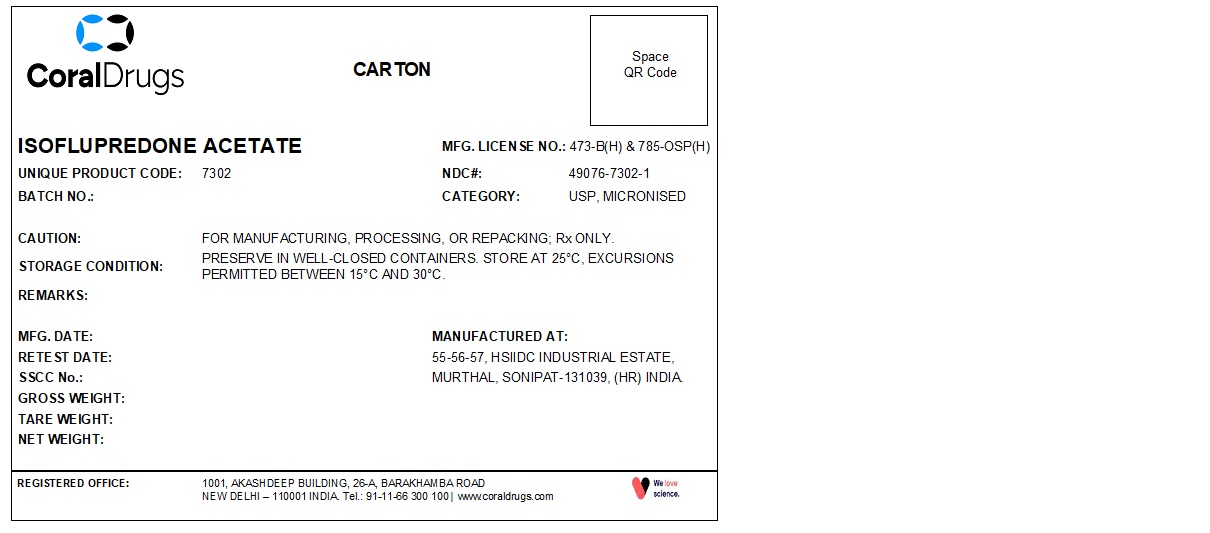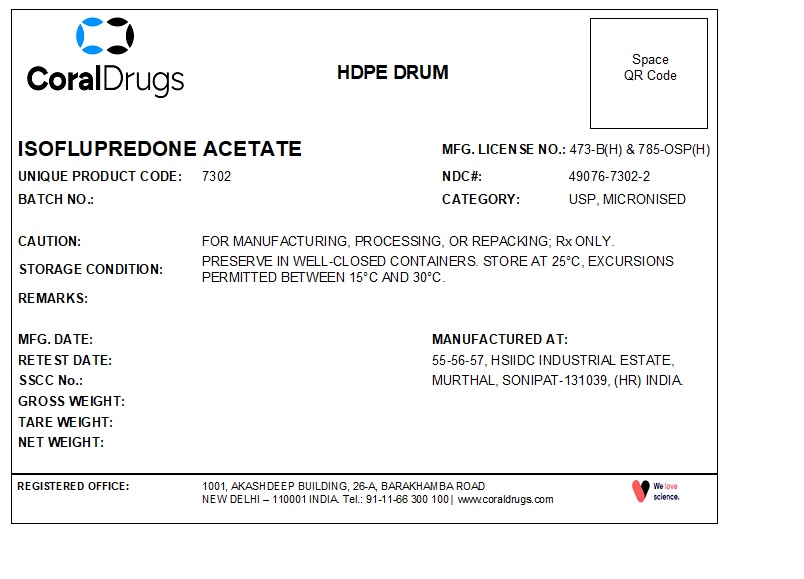 DRUG LABEL: Isoflupredone Acetate
NDC: 49076-7302 | Form: POWDER
Manufacturer: Coral Drugs Private Limited
Category: other | Type: BULK INGREDIENT - ANIMAL DRUG
Date: 20251113

ACTIVE INGREDIENTS: Isoflupredone Acetate 1 kg/1 kg

Isoflupredone Acetate